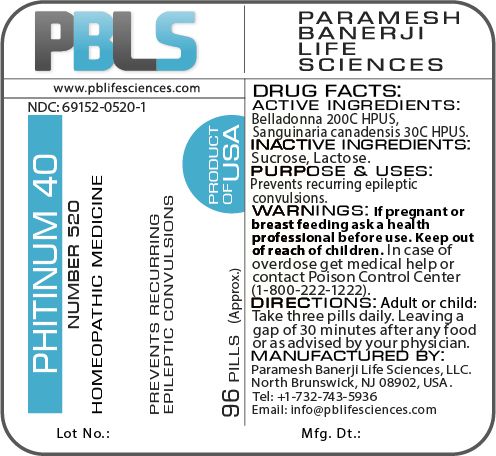 DRUG LABEL: Phitinum 40 (Number 520)
NDC: 69152-0520 | Form: PELLET
Manufacturer: Paramesh Banerji Life Sciences LLC
Category: homeopathic | Type: HUMAN OTC DRUG LABEL
Date: 20180202

ACTIVE INGREDIENTS: ATROPA BELLADONNA 200 [hp_C]/1 1; SANGUINARIA CANADENSIS ROOT 30 [hp_C]/1 1
INACTIVE INGREDIENTS: SUCROSE; LACTOSE

DRUG FACTS: Active Ingredients

Belladonna 200C HPUS, Sanguinaria canadensis 30C HPUS

Inactive Ingredients

Sucrose, Lactose

Purpose

Prevents recurring epileptic convulsions

Uses

Prevents recurring epileptic convulsions

Warnings

If pregnant or breast feeding ask a health professional before use.

Keep out of reach of children. In case of overdose, get medical help or contact a Poison Control Center (1-800-222-1222) right away.

Direction

Adult or child: Take three pills daily. Leaving a gap of 30 minutes after any food or as advised by your physician.

Manufactured by

Paramesh Banerji Life Sciences, LLC.

North Brunswick, NJ 08902, USA.

Tel: +1-732-743-5936

Email: info@pblifesciences.com

Principal Display Panel

NDC: 69152-0520-1

Phitinum 40

Number 520

Homeopathic Medicine

Prevents recurring epileptic convulsions

96 Pills (Approx.)

Product of USA